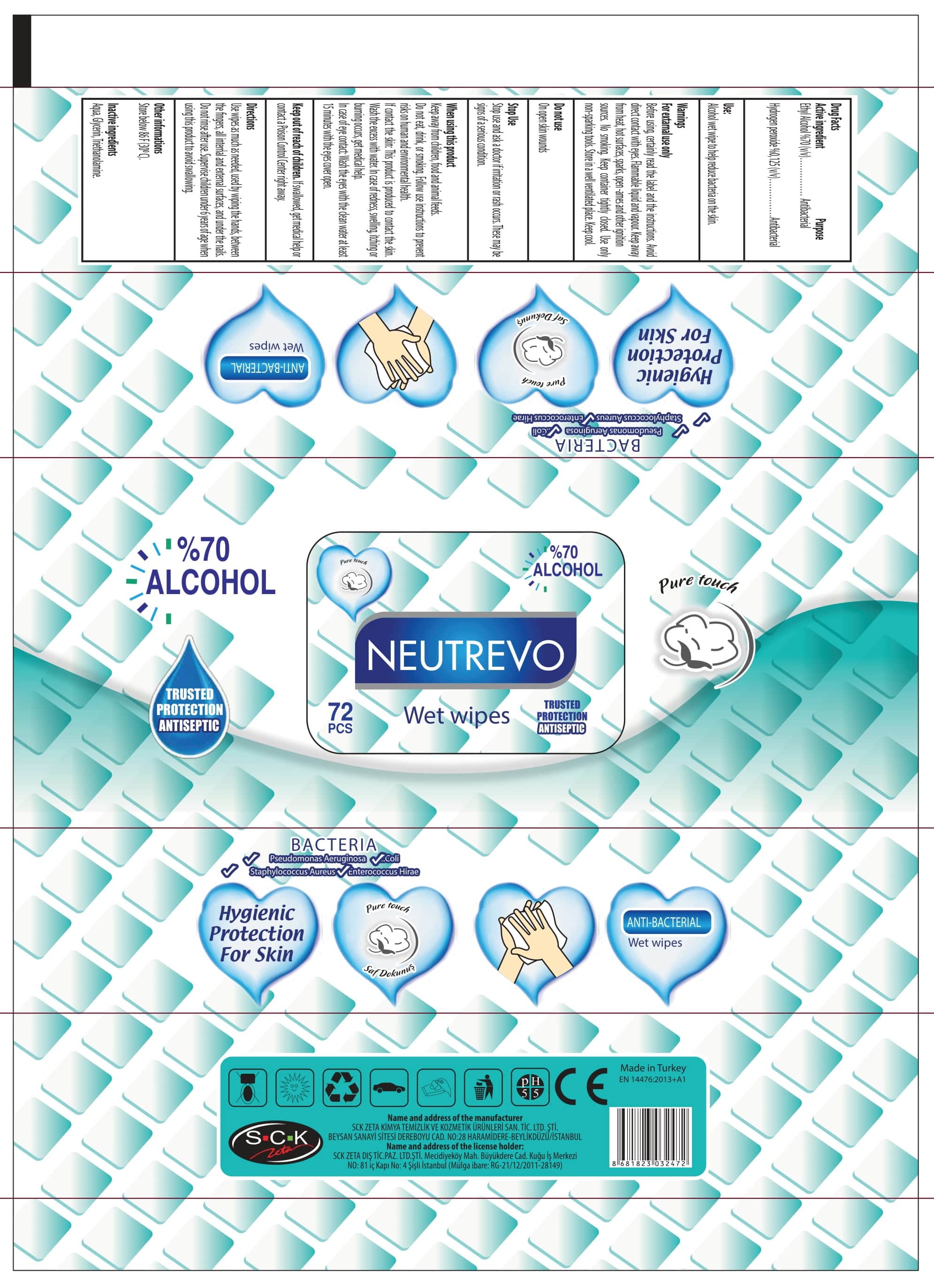 DRUG LABEL: Neutrevo Alcohol Wet Wipes
NDC: 86818-005 | Form: CLOTH
Manufacturer: SCK ZETA DIS TICARET
Category: otc | Type: HUMAN OTC DRUG LABEL
Date: 20201007

ACTIVE INGREDIENTS: HYDROGEN PEROXIDE 0.125 mL/100 mL; ALCOHOL 70 mL/100 mL
INACTIVE INGREDIENTS: GLYCERIN; WATER; TROLAMINE

NEUTREVO ALCOHOL WET WIPES

This is a hand sanitizer manufactured according to the Temporary Policy for Preparation of Certain Alcohol-Based Hand Sanitizer Products During the Public Health Emergency (CoViD-19); Guidance for Industry.

The hand sanitizer is manufactured using only the following United States Pharmacopoeia (USP) grade ingredients in the preparation of the product (percentage in final product formulation) consistent with World Health Organization (WHO) recommendations:

1. Alcohol (ethanol) (USP or Food Chemical Codex (FCC) grade) (70%, volume/volume (v/v)) in an aqueous solution denatured according to Alcohol and Tobacco Tax and Trade Bureau regulations in 27 CFR part 20.
2. Glycerol .
3. Hydrogen peroxide (0.125% v/v).
4. Triethanolamine
5. Sterile distilled water or boiled cold water.

The firm does not add other active or inactive ingredients. Different or additional ingredients may impact the quality and potency of the product.

Active Ingredient(s)

Alcohol 70% v/v. Purpose: Antibacterial

Hydrogen Peroxide 0.125 v/v Purpose: Antibacterial

Purpose

Antibacterial - Antiseptic

Use

Alcohol wet wipe to help reduce bacteria on the skin.

Warnings

For external use only. Before using certainly read the label and the instructions. Avoid direct contact with eyes. Flammable liquid and vapour. Keep away from heat , hot surfaces, sparks, open-ames and other ignition sources. No smoking. Keep container tightly closed. Use only non-sparking tools. Store in a well ventilated place. Keep cool

Do not use

- on open skin wounds

When using this product Keep out of reach of children, food and animal feeds. Do not eat, dirnk and smoking. Follow use instructions to prevent risks on human and environmental health.If contact the skin: This product is produced to contact the skin. Wash the excess with water. In case of redness, swelling, itching or burning occurs, get medical help.In case of eye contact: wash the eyes with the clean water at least 15 minutes with the eyes cover open. If swallowed shake the mouth with water. Do not induce vomiting. Immediately apply to the doctor and show him the label of the product.

Stop use and ask a doctor if irritation or rash occurs. These may be signs of a serious condition.

Keep out of reach of children. If swallowed, get medical help or contact a Poison Control Center right away.

Directions

- Use wipes as much as needed, used by wiping the hands, between the fingers, all internal and external surfaces and under the nails. Do not rinse after use.
- Supervise children under 6 years of age when using this product to avoid swallowing.

Other information

- Store between 30C (86F)

Inactive ingredients

glycerin, triethanolamin, water